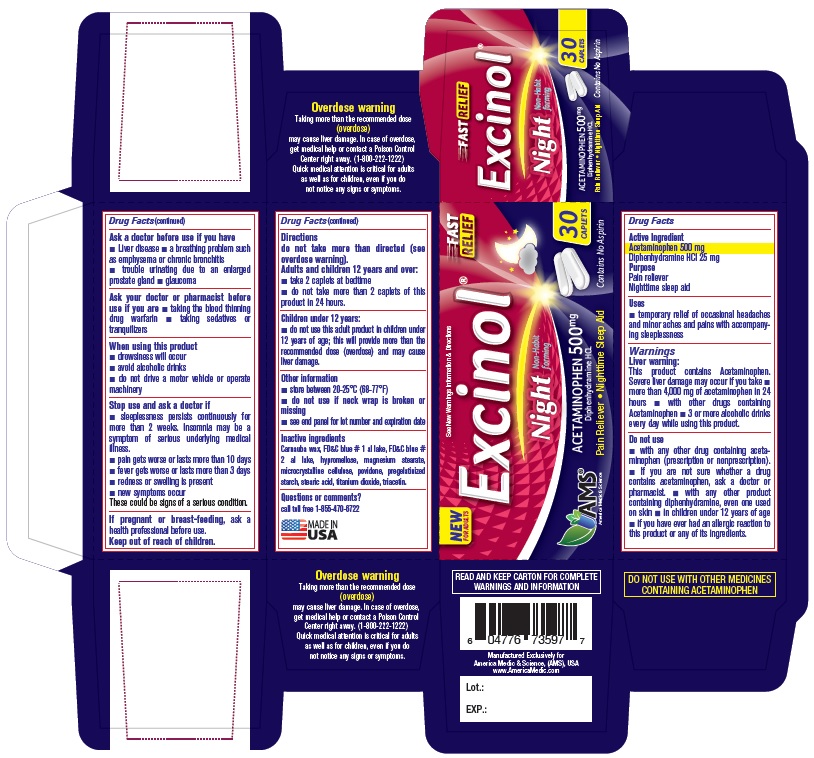 DRUG LABEL: Excinol Night (Acetaminophen)
NDC: 49638-105 | Form: TABLET, DELAYED RELEASE
Manufacturer: America Medic & Science, LLC
Category: otc | Type: HUMAN OTC DRUG LABEL
Date: 20190122

ACTIVE INGREDIENTS: ACETAMINOPHEN 500 mg/1 1; DIPHENHYDRAMINE HYDROCHLORIDE 25 mg/1 1
INACTIVE INGREDIENTS: CARNAUBA WAX; FD&C BLUE NO. 1; FD&C BLUE NO. 2; HYPROMELLOSE, UNSPECIFIED; MAGNESIUM STEARATE; MICROCRYSTALLINE CELLULOSE; POVIDONE; STARCH, CORN; STEARIC ACID; TITANIUM DIOXIDE; TRIACETIN

Excinol Night (Acetaminophen)
500 mg

Excinol Night (Acetaminophen) 500 mg

Drug Facts

Active Ingredient

Acetaminophen 500 mg

Diphenhydramine HCl 25 mg

Purpose

Pain reliever

Night time sleep aid

Uses

- temporary relief of occasional headaches and minor aches and pains with accompanying sleeplessness

Warnings

Liver warning: This product contains Acetaminophen. Severe liver damage may occur if you take

- more than 4,000 mg of acetaminophen in 24 hours
- with other drugs containing Acetaminophen
- 3 or more alcoholic drinks every day while using this product.

Do not use

- with any other drug containing acetaminophen (prescription or nonprescription).
- If you are not sure whether a drug contains acetaminophen, ask a doctor or pharmacist.
- with any other product containing diphenhydramine, even one used on skin
- in children under 12 years of age
- if you have ever had an allergic reaction to this product or any of its ingredients.

Ask a doctor before use if you have

- Liver disease
- a breathing problem such as emphysema or chronic bronchitis
- trouble urinating due to an enlarged prostate gland
- glaucoma

ASK DOCTOR/PHARMACIST

Ask your doctor or pharmacist before use if you are

- taking the blood thinning drug warfarin
- taking sedatives or tranquilizers

When using this product

- drowsiness will occur
- avoid alcoholic drinks
- do not drive a motor vehicle or operate machinery

Stop use and ask a doctor if

- sleeplessness persists continuously for more than 2 weeks. Insomnia may be a symptom of serious underlying medical illness.
- pain gets worse or lasts more than 10 days
- fever gets worse or lasts more than 3 days
- redness or swelling is present
- new symptoms occur

These could be signs of a serious condition.

PREGNANCY OR BREAST FEEDING

If pregnant or breast-feeding, ask a health professional before use.

Keep out of reach of children.

Directions

do not take more than directed (see overdose warning).

Adults and children 12 years and over:

- take 2 caplets at bedtime
- do not take more than 2 caplets of this product in 24 hours.

Children under 12 years:

- do not use this adult product in children under 12 years of age; this will provide more than the recommended dose (overdose) and may cause liver damage.

Other information

- store between 20-25°C (68-77°F)
- do not use if neck wrap is broken or missing
- see end panel for lot number and expiration date

Inactive ingredients

Carnauba wax, FD&C blue# 1 al lake, FD&C blue# 2 al lake, hypromellose, magnesium stearate, microcrystalline cellulose, povidone, pregelatinized starch, stearic acid, titanium dioxide, triacetin.

Questions or comments?

call toll free 1-855-470-6722